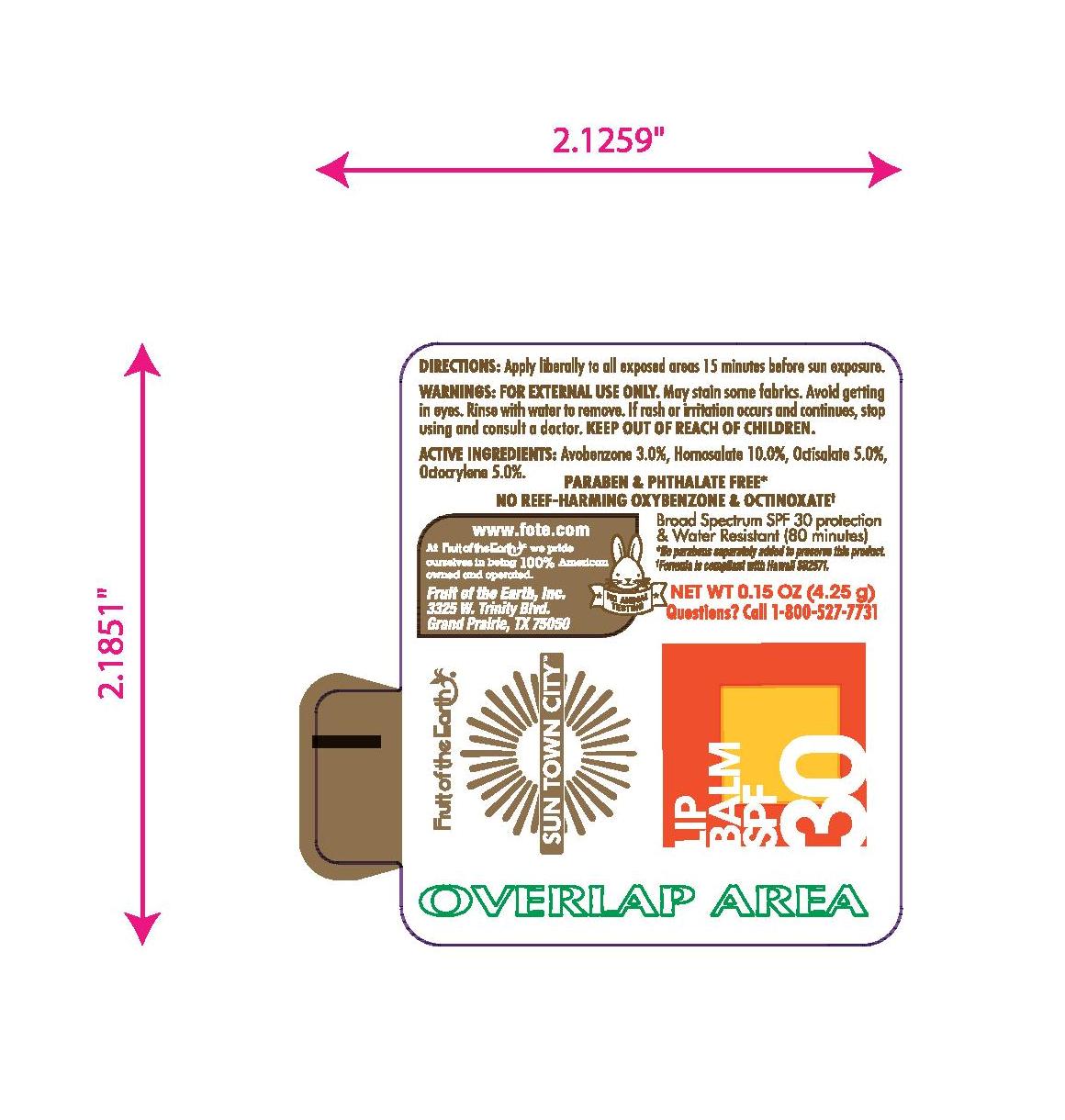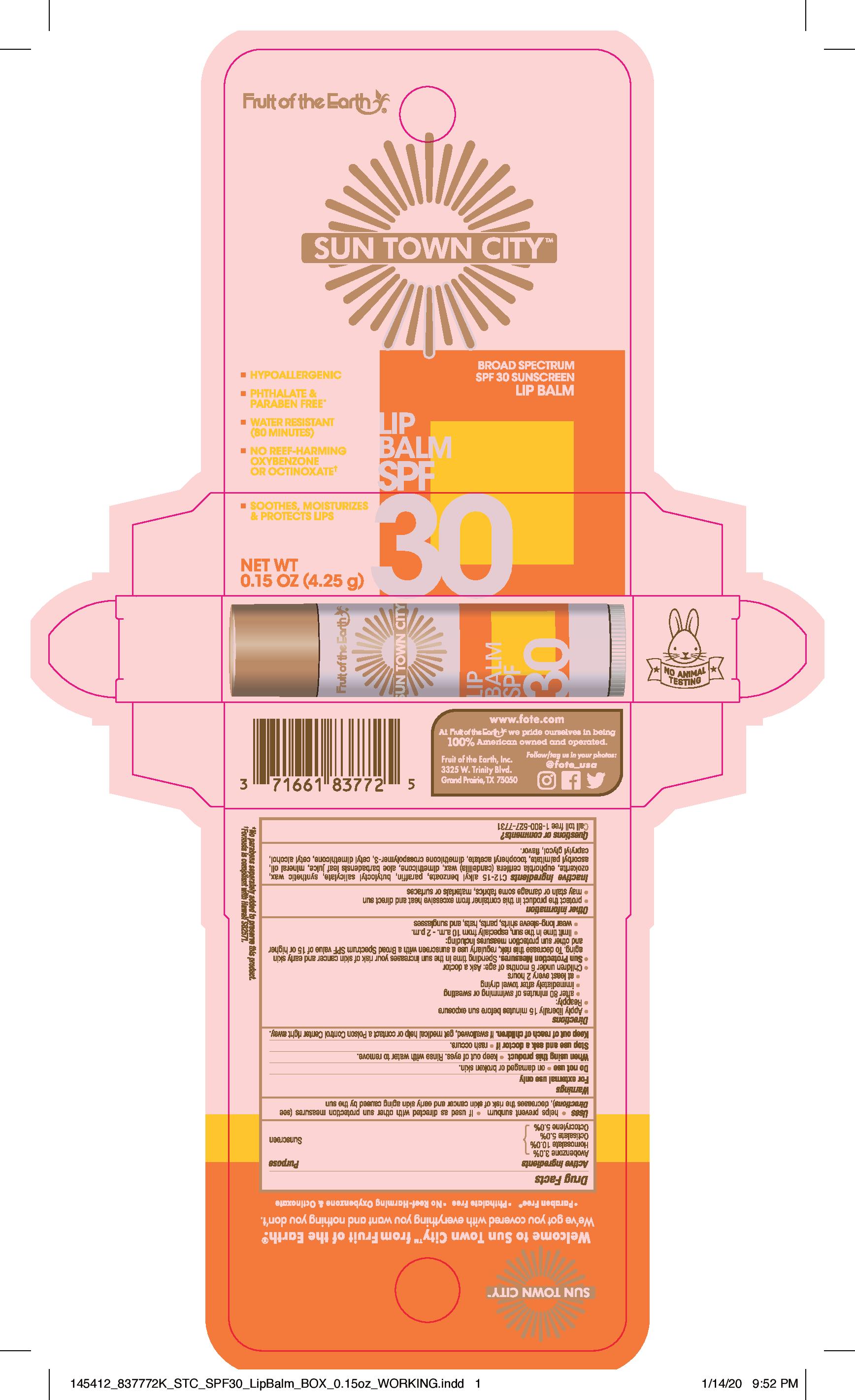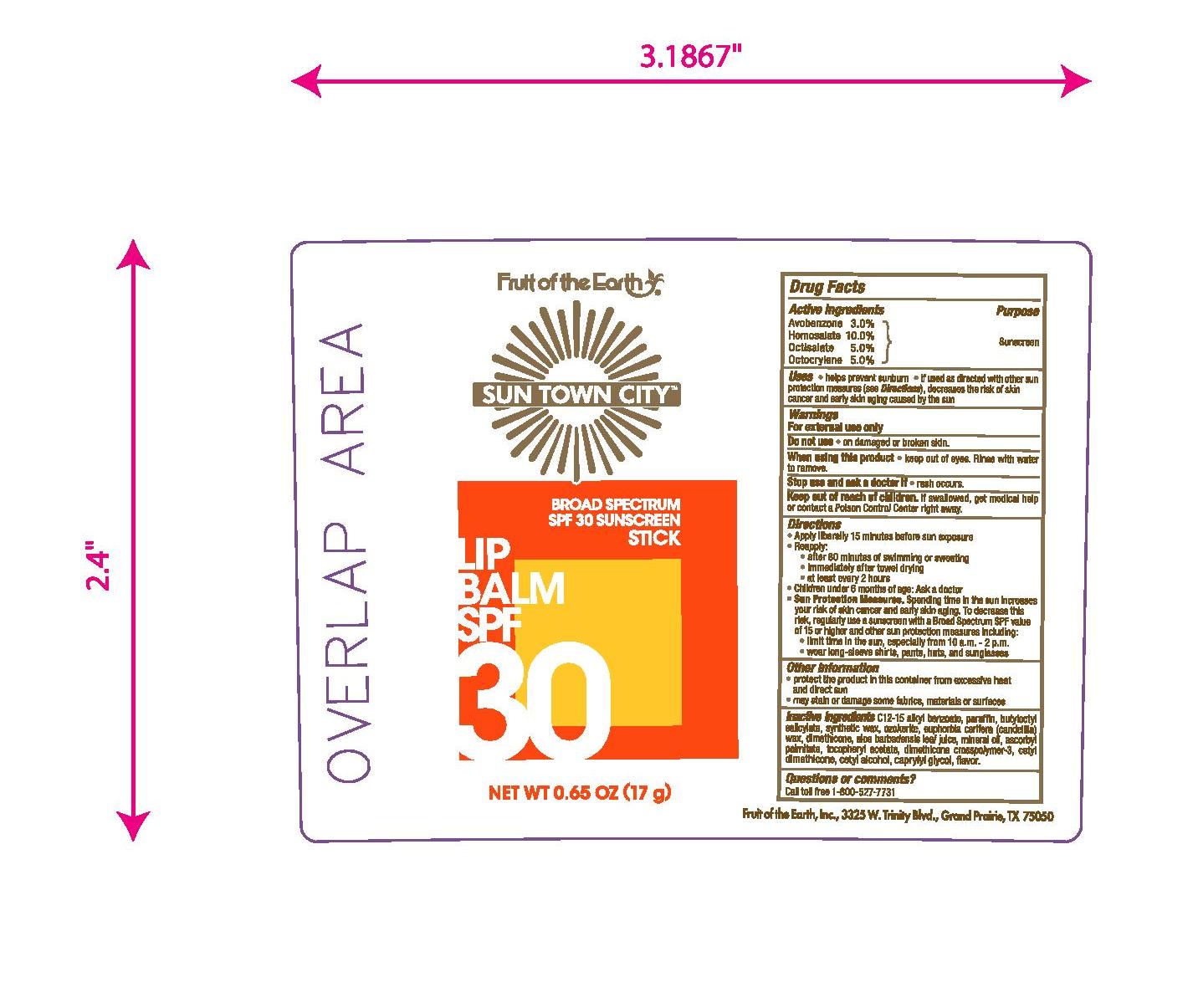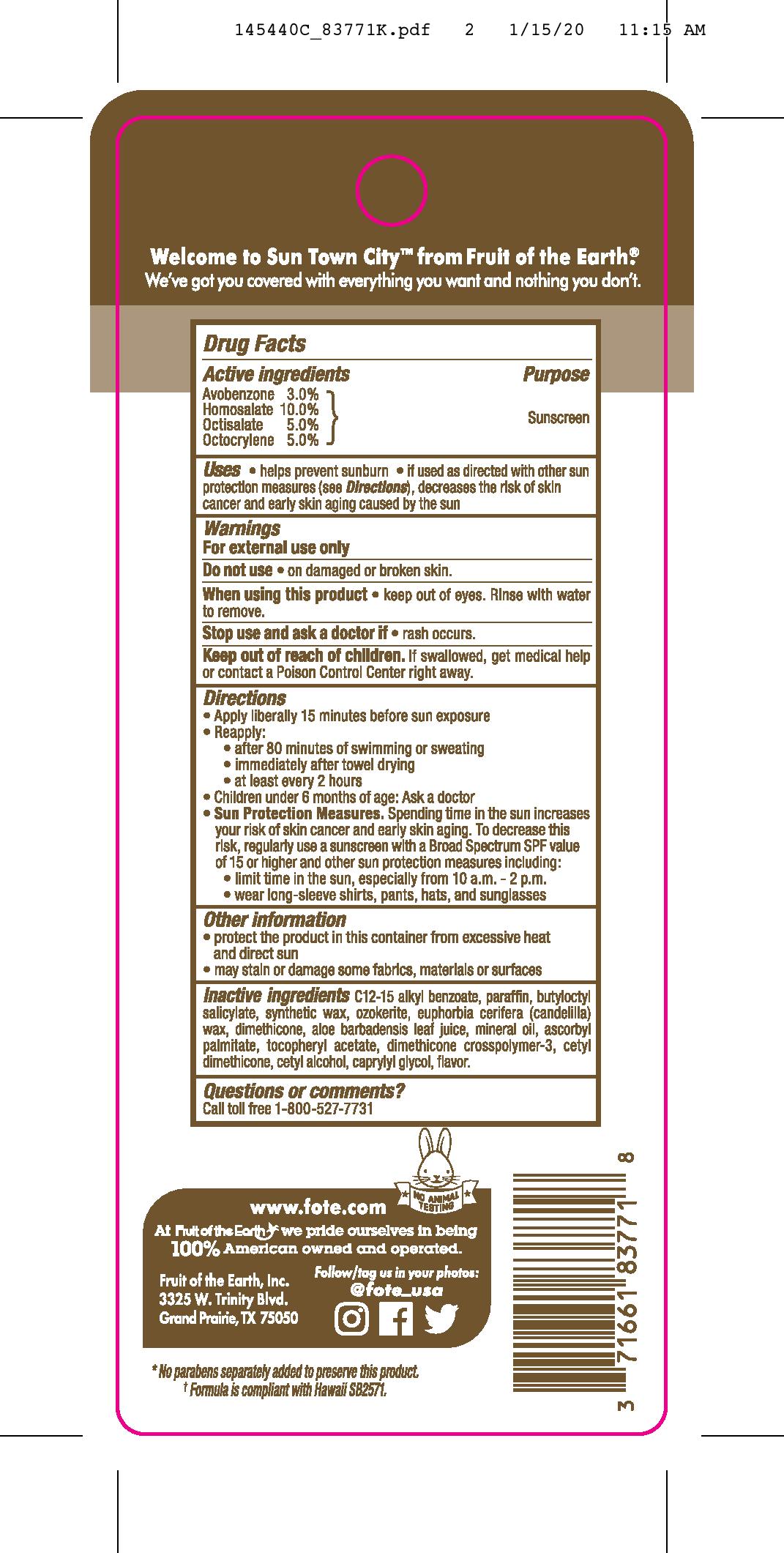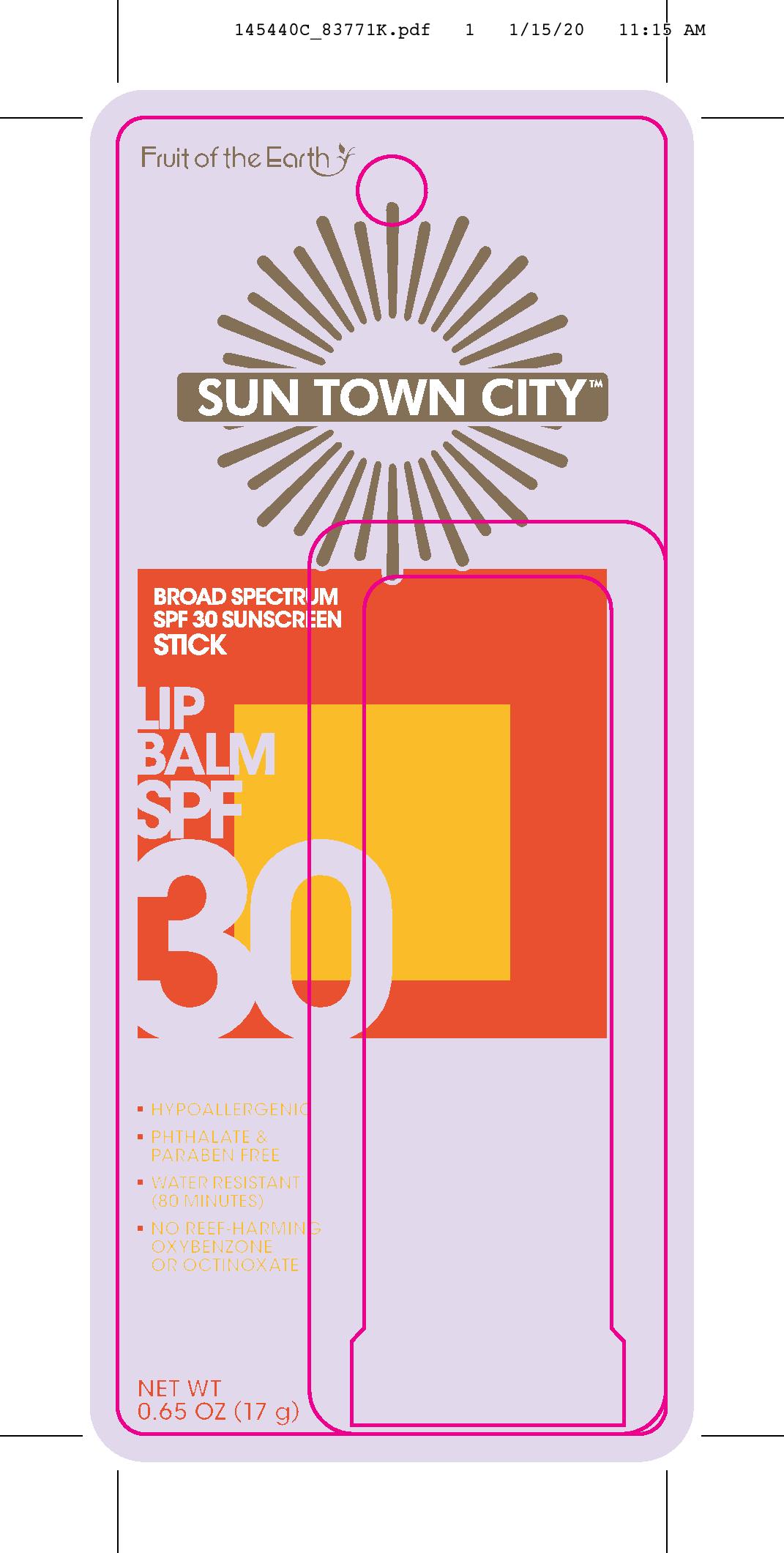 DRUG LABEL: Fruit of the Earth
NDC: 62217-316 | Form: STICK
Manufacturer: Fruit of the Earth, Inc.
Category: otc | Type: HUMAN OTC DRUG LABEL
Date: 20241018

ACTIVE INGREDIENTS: OCTISALATE 50 mg/1 g; OCTOCRYLENE 50 mg/1 g; AVOBENZONE 30 mg/1 g; HOMOSALATE 100 mg/1 g
INACTIVE INGREDIENTS: ALKYL (C12-15) BENZOATE; PARAFFIN; BUTYLOCTYL SALICYLATE; CANDELILLA WAX; CERESIN; YELLOW WAX; CETYL DIMETHICONE 25; CAPRYLYL GLYCOL; CETYL ALCOHOL; MINERAL OIL; ASCORBYL PALMITATE; .ALPHA.-TOCOPHEROL ACETATE; ALOE VERA LEAF; DIMETHICONE

Fruit of the Earth Sun Town City Lip Balm SPF 30 Sunscreen Stick

Active ingredients

Avobenzone 3.0%, Homosalate 10.0%, Octisalate 5.0%, Octocrylene 5.0%

Purpose

Sunscreen

Uses

• helps prevent sunburn • if used as directed with other sun protection measures (see Directions), decreases the risk of skin cancer and early skin aging casued by the sun

Warnings

For external use only

Do not use • on damaged or broken skin.

When using this product • keep out of eyes. Rinse with water to remove.

Stop use and ask a doctor if • rash occurs.

Keep out of reach of children. If swallowed, get medical help or contact a Poison Control Center right away.

Directions

- Apply liberally 15 minutes before sun exposure
- Reapply:

• after 80 minutes of swimming or sweating

• immediately after towel drying

• at least every 2 hours

- Children under 6 months of age: Ask a doctor
- Sun Protection Measures. Spending time in the sun increases your risk of skin cancer and early skin aging. To decrease this risk, regularly use a sunscreen with a Broad Spectrum SPF value of 15 or higher and other sun protection measures including:

• limit time in the sun, especially from 10 a.m.-2 p.m.

• wear long-sleeved shirts, pants, hats, and sunglasses

Other information

- protect the product in this container from excessive heat and direct sun
- may stain or damage some fabrics, materials or surfaces

Inactive ingredients

C12-15 alkyl benzoate, paraffin, butyloctyl salicylate, synthetic wax, ozokerite, euphorbia cerifera (candelilla) wax, dimethicone, aloe barbadensis leaf juice, mineral oil, ascorbyl palmitate, tocopheryl acetate, dimethicone crosspolymer-3, cetyl dimethicone, cetyl alcohol, caprylyl glycol, flavor.

Questions of comments?

Call toll free 1-800-527-7731

PACKAGE LABEL

Fruit of the Earth Sun Town City Lip Balm SPF 30 Sunscreen Stick

0.65 OZ (17g)

NDC 62217-316-84

NDC 62217-316-85

Fruit of the Earth Sun Town City Lip Balm SPF 30 Sunscreen Stick

0.15 OZ (4.25g)

NDC 62217-316-58

NDC 62217-316-59